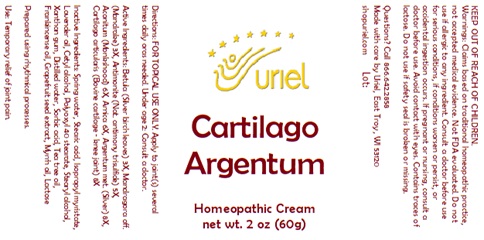 DRUG LABEL: Cartilago Argentum
NDC: 48951-3260 | Form: CREAM
Manufacturer: Uriel Pharmacy Inc.
Category: homeopathic | Type: HUMAN OTC DRUG LABEL
Date: 20251118

ACTIVE INGREDIENTS: ACONITUM NAPELLUS 6 [hp_X]/1 g; ARNICA MONTANA 6 [hp_X]/1 g; SILVER 8 [hp_X]/1 g; BOS TAURUS CARTILAGE 8 [hp_X]/1 g; BETULA PUBESCENS LEAF 3 [hp_X]/1 g; ANTIMONY TRISULFIDE 5 [hp_X]/1 g; MANDRAGORA OFFICINARUM ROOT 3 [hp_X]/1 g
INACTIVE INGREDIENTS: ISOPROPYL MYRISTATE; STEARIC ACID; FRANKINCENSE OIL; WATER; SORBIC ACID; MYRRH OIL; LAVENDER OIL; CETYL ALCOHOL; POLYOXYL 40 STEARATE; STEARYL ALCOHOL; XANTHAN GUM; TEA TREE OIL; CITRUS PARADISI SEED; LACTOSE, UNSPECIFIED FORM

Cartilago Argentum

INDICATIONS AND USAGE

Directions:FOR TOPICAL USE ONLY.

DOSAGE AND ADMINISTRATION

Apply to joint(s) several times daily or as needed. Under age 2: Consult a doctor.

ACTIVE INGREDIENT

Active Ingredients: Betula (Silver birch leaves) 3X, Mandragora off. (Mandrake) 3X, Antimonite (Nat. antimony trisulfide) 5X, Aconitum (Monkshood) 6X, Arnica 6X, Argentum met. (Silver) 8X, Cartilago articularis (Bovine cartilage - knee joint) 8X

INACTIVE INGREDIENT

Inactive Ingredients: Spring water, Stearic acid, Isopropyl myristate, Lavender oil, Cetyl alcohol, Polyoxyl 40 stearate, Stearyl alcohol, Xanthan gum, Distilled water, Sorbic acid, Tea tree oil, Frankincense oil, Grapefruit seed extract, Myrrh oil, Lactose

Prepared using rhythmical processes.

PURPOSE

Use: Temporary relief of joint pain.

KEEP OUT OF REACH OF CHILDREN.

WARNINGS

Warnings: Claims based on traditional homeopathic practice, not accepted medical evidence. Not FDA evaluated. Do not use if allergic to any ingredient. Consult a doctor before use for serious conditions, if conditions worsen or persist, or accidental ingestion occurs. If pregnant or nursing, consult a doctor before use. Avoid contact with eyes. Contains traces of lactose. Do not use if safety seal is broken or missing.

Questions? Call 866.642.2858
Made with care by Uriel, East Troy, WI 53120
shopuriel.com Lot: